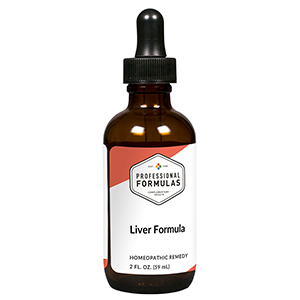 DRUG LABEL: Liver Formula
NDC: 63083-2102 | Form: LIQUID
Manufacturer: Professional Complementary Health Formulas
Category: homeopathic | Type: HUMAN OTC DRUG LABEL
Date: 20190815

ACTIVE INGREDIENTS: SALVIA MILTIORRHIZA ROOT 1 [hp_X]/59 mL; CROCUS SATIVUS FLOWER 1 [hp_X]/59 mL; SCUTELLARIA BAICALENSIS ROOT 1 [hp_X]/59 mL; LEUZEA RHAPONTICA ROOT 1 [hp_X]/59 mL; AKEBIA STEM 1 [hp_X]/59 mL; GARDENIA JASMINOIDES FRUIT 1 [hp_X]/59 mL; PAEONIA LACTIFLORA ROOT 1 [hp_X]/59 mL; FRITILLARIA DELAVAYI WHOLE 1 [hp_X]/59 mL; ANGELICA ACUTILOBA ROOT 3 [hp_X]/59 mL
INACTIVE INGREDIENTS: ALCOHOL; WATER

C102

ACTIVE INGREDIENTS

Dan-Shen 1X
Hong-Hua 1X
Huang-Qin 1X
Lou-Lu 1X
Mu-Tung 1X
Shan-Zhi-Zi 1X
Shao-Yao 1X
Suo-Sha 1X
Tang-Kuei 3X

QUESTIONS

Professional Formulas

PO Box 2034 Lake Oswego, OR 97035

INDICATIONS

For the temporary relief of minor abdominal pain or swelling, fatigue, irritability, constipation, loss of appetite, or low energy level.*

PURPOSE

*Claims based on traditional homeopathic practice, not accepted medical evidence. Not FDA evaluated.

WARNINGS

Severe or persistent symptoms may be serious. Consult a doctor promptly. Keep out of the reach of children. In case of overdose, get medical help or contact a poison control center right away. If pregnant or breastfeeding, ask a healthcare professional before use.

Keep out of the reach of children.

PREGNANCY OR BREAST FEEDING

If pregnant or breastfeeding, ask a healthcare professional before use.

DIRECTIONS

Place drops under tongue 30 minutes before/after meals. Adults and children 12 years and over: Take 10 drops up to 3 times per day. Consult a physician for use in children under 12 years of age.

OTHER INFORMATION

Tamper resistant. If seal is broken, do not use. After opening, close container tightly and store at room temperature away from heat.

INACTIVE INGREDIENTS

20% ethanol, purified water.

LABEL

Est 1985

Professional Formulas

Complementary Health

Liver Formula

Homeopathic Remedy

2 FL. OZ. (59 mL)